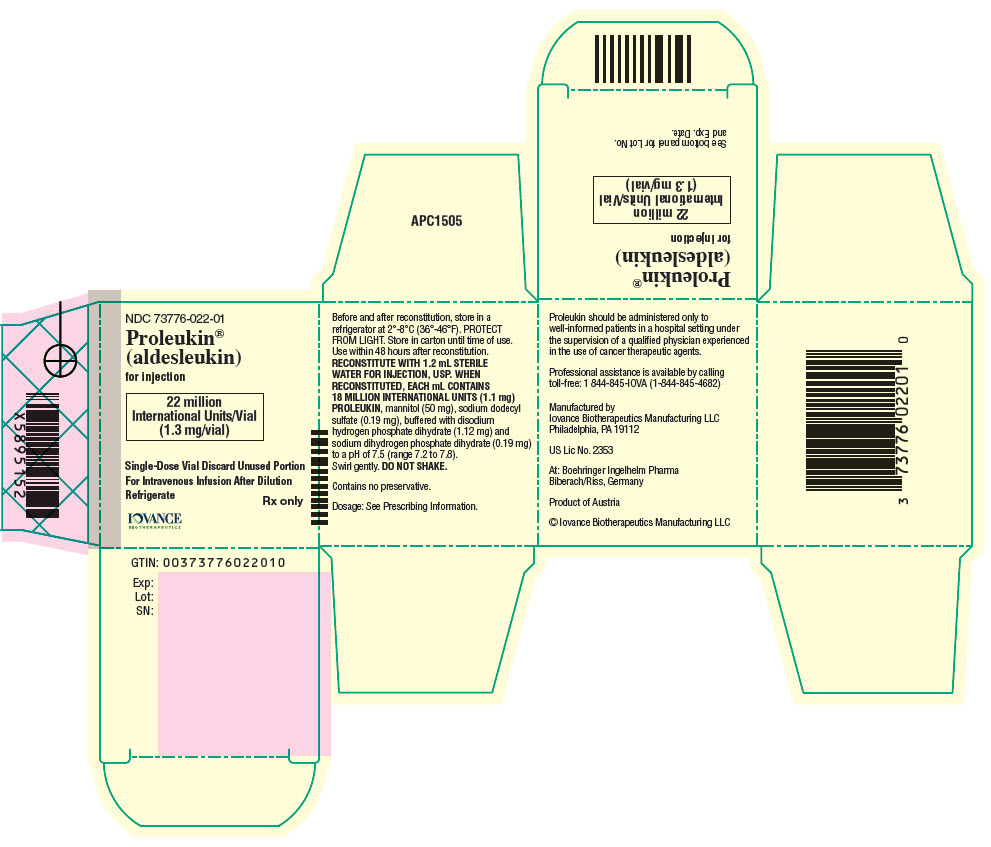 DRUG LABEL: PROLEUKIN
NDC: 73776-022 | Form: INJECTION, POWDER, LYOPHILIZED, FOR SOLUTION
Manufacturer: Iovance Biotherapeutics, Inc
Category: prescription | Type: HUMAN PRESCRIPTION DRUG LABEL
Date: 20241220

ACTIVE INGREDIENTS: ALDESLEUKIN 1.1 mg/1 mL
INACTIVE INGREDIENTS: MANNITOL; SODIUM PHOSPHATE, MONOBASIC, UNSPECIFIED FORM; SODIUM LAURYL SULFATE; SODIUM PHOSPHATE, DIBASIC, UNSPECIFIED FORM; WATER

HIGHLIGHTS OF PRESCRIBING INFORMATION

These highlights do not include all the information needed to use PROLEUKIN®safely and effectively. See full prescribing information for PROLEUKIN.
PROLEUKIN (aldesleukin) for injection, for intravenous use
Initial U.S. Approval: 1992

WARNING: CAPILLARY LEAK SYNDROME (CLS), NEUROLOGIC TOXICITIES and SERIOUS INFECTIONS

WARNING: CAPILLARY LEAK SYNDROME (CLS), NEUROLOGIC TOXICITY, AND SERIOUS INFECTIONS

See full prescribing information for complete boxed warning.

- Capillary Leak Syndrome (CLS) including life-threatening or fatal reactions, has occurred in patients treated with Proleukin. Administer Proleukin in a hospital setting with an intensive care unit. Withhold or discontinue Proleukin as recommended. (2.4, 4, 5.1)
- Neurologic toxicities, which may be life-threatening or result in coma or permanent neurological deficits, have occurred in patients treated with Proleukin. Withhold or discontinue Proleukin as recommended. (2.4, 5.2)
- Serious infections including sepsis and bacterial endocarditis have occurred in patients treated with Proleukin. Treat preexisting bacterial infections prior to initiating Proleukin and withhold Proleukin as recommended. (2.4, 5.3)

1 INDICATIONS AND USAGE

Proleukin is a lymphocyte growth factor indicated for:

- The treatment of adults with metastatic renal cell carcinoma. (1.1)
- The treatment of adults with metastatic melanoma. (1.2)

2 DOSAGE AND ADMINISTRATION

Administer Proleukin in an inpatient hospital setting with an intensive care facility.

- Evaluate cardiovascular, pulmonary, neurologic and renal function before beginning Proleukin. (2.1)
- See Full Prescribing Information for Premedication and Supportive medications. (2.3)
- Recommended dosage: 600,000 IU/kg (0.037 mg/kg) every 8 hours by a 15-minute intravenous infusion for a maximum of 14 doses. Following 9 days of rest, repeat the schedule for a maximum of another 14 doses (total of 28 doses per course, as tolerated). (2.2)
- Evaluate patients approximately 4 weeks after completion of a course of therapy and again immediately prior to the start of the next course. (2.2)
- Dose modification for toxicity should be accomplished by withholding or interrupting a dose. (2.4)
- Follow reconstitution and dilution procedures. (2.5)

3 DOSAGE FORMS AND STRENGTHS

For Injection: 22 million International Units (1.3 mg) lyophilized powder in a single-dose vial. (3)

4 CONTRAINDICATIONS

- Hypersensitivity to aldesleukin. (4)
- Organ allografts. (4)
- Significant organ impairment. (4)

5 WARNINGS AND PRECAUTIONS

- Renal Toxicity:Monitor renal function at baseline and throughout treatment. Withhold Proleukin or permanently discontinue, based on severity. (2.4, 5.4)
- Immune-mediated Adverse Reactions:Exacerbation of pre-existing autoimmune disease or initial presentation of autoimmune and inflammatory disorders can occur in any system or tissue. Proleukin may increase the risk of allograft rejection in transplant patients. Monitor patients and treat as indicated. (5.5)
- Severe Hypersensitivity Reaction:Permanently discontinue Proleukin for severe hypersensitivity reactions. (4, 5.9)
- Embryo-Fetal Toxicity: May cause fetal harm. Advise females of reproductive potential of potential risk to a fetus and to use effective contraception. (5.6, 8.1, 8.3)

6 ADVERSE REACTIONS

Most common (≥ 30%) adverse reactions including laboratory abnormalities are hypotension, hyperbilirubinemia, dyspnea, rash, diarrhea, oliguria, chills, vomiting, thrombocytopenia, nausea, confusional state and increased creatinine. (6.1)

To report SUSPECTED ADVERSE REACTIONS, contact Iovance Biotherapeutics Manufacturing LLC. at 1 844-845-IOVA or FDA at 1-800-FDA-1088 or www.fda.gov/medwatch.

7 DRUG INTERACTIONS

See Full Prescribing Information for important drug interactions. (7)

8 USE IN SPECIFIC POPULATIONS

- Pregnancy: May cause fetal harm. (8.1)
- Lactation: Advise not to breastfeed. (8.2)

FULL PRESCRIBING INFORMATION

WARNING: CAPILLARY LEAK SYNDROME (CLS), NEUROLOGIC TOXICITIES and SERIOUS INFECTIONS

- Capillary leak syndrome (CLS), including life threatening or fatal reactions, has occurred in patients treated with Proleukin. Do not administer Proleukin to patients with significant cardiac, pulmonary, renal, and hepatic impairment. Administer Proleukin in a hospital setting with an intensive care facility. Withhold or discontinue Proleukin as recommended [see Dosage and Administration (2.4), Contraindications (4), Warnings and Precautions (5.1)] .
- Neurologic toxicities, which may be life-threatening or result in coma or permanent neurological deficits, have occurred in patients treated with Proleukin. Withhold or discontinue Proleukin as recommended [see Dosage and Administration (2.4), Warnings and Precautions (5.2)] .
- Serious Infections including sepsis and bacterial endocarditis have occurred in patients treated with Proleukin. Treat pre-existing bacterial infections prior to initiation of Proleukin therapy and withhold Proleukin as recommended [see Dosage and Administration (2.4), Warnings and Precautions (5.3)] .

1 INDICATIONS AND USAGE

1.1 Metastatic Renal Cell Carcinoma

Proleukin is indicated for the treatment of adults with metastatic renal cell carcinoma (RCC).

1.2 Metastatic Melanoma

Proleukin is indicated for the treatment of adults with metastatic melanoma.

2 DOSAGE AND ADMINISTRATION

2.1 Recommended Evaluation and Testing Before Initiating Proleukin

Conduct baseline hematologic, chemistry, renal and hepatic function tests. Additionally, evaluate cardiac ejection fraction, coronary artery disease as appropriate, pulmonary function with PFTs, and evaluate for renal, hepatic, and CNS impairment prior to initiating treatment with Proleukin [see Contraindications (4), Warnings and Precautions (5.1, 5.2)].

Verify pregnancy status of females of reproductive potential prior to initiating Proleukin [see Warnings and Precautions (5.6), Use in Specific Populations (8.1, 8.3)].

2.2 Recommended Dosage

Administer Proleukin in an inpatient hospital setting. An intensive care facility with specialists skilled in cardiopulmonary or intensive care medicine must be available [see Warnings and Precautions (5.1)] .

The recommended dosage of Proleukin for metastatic renal cell carcinoma and metastatic melanoma is described in Table 1.

Administer Proleukin as an intravenous infusion after dilution [see Dosage and Administration (2.5)] .

Administer pre-infusion medications and supportive treatment, as appropriate, prior to and during each infusion [see Dosage and Administration (2.3)]. Discontinue Proleukin for unacceptable toxicity [see Dosage and Administration (2.4)].

Table 1: Recommended Dosage of Proleukin
Each course of therapy consists of the following:
Cycle 1 | Days 1-5 | 600,000 IU/kg (0.037 mg/kg) every 8 hours; maximum of 14 doses [A maximum of 28 doses (2 cycles) per treatment course]
Rest period | Days 6-14
Cycle 2 | Days 15-19 | 600,000 IU/kg (0.037 mg/kg) every 8 hours; maximum of 14 doses

Evaluate patients for response approximately 4 weeks after completion of a course of therapy and again immediately prior to the scheduled start of the next treatment course.

Additional courses of treatment may be administered to patients if there is a treatment response following the last course, and the patient did not experience any adverse reactions in previous course(s) that led to permanent discontinuation [see Dosage and Administration (2.4)].

Separate each treatment course by a rest period of at least 7 weeks from the date of hospital discharge.

2.3 Premedication and Supportive Medications

Premedicate patients with an antipyretic immediately prior to beginning Proleukin. Continue antipyretics during treatment as needed for fever [see Warnings and Precautions (5.1, 5.10)].

Administer prophylactic antibiotics per institutional guidelines prior to beginning Proleukin and throughout the treatment course for patients with indwelling central catheters [see Warnings and Precautions (5.3)].

Administer prophylactic medication for gastrointestinal irritation and bleeding during each Proleukin treatment course [see Adverse Reactions (6.1)].

Additional medications may be needed if patients experience hypotension, dyspnea, rigors, nausea, diarrhea, pruritis, or dermatitis [see Warnings and Precautions (5.1, 5.8, 5.9)].

2.4 Dosage Modifications for Adverse Reactions

No dose reduction for Proleukin is recommended for adverse reactions. In general, withhold or interrupt a dose or permanently discontinue Proleukin based on the severity of the adverse reaction as described in Table 2.

Table 2: Recommended Dosage Modifications for Adverse Reactions
Adverse Reaction | Severity | Dosage Modification
Cardiovascular [see Warnings and Precautions (5.1)] | - Atrial fibrillation, - Supraventricular tachycardia, or - Bradycardia that requires treatment or is recurrent or persistent - Decrease in systolic blood pressure to <90 mmHg | Withhold until patient is asymptomatic with full recovery to normal sinus rhythm
Cardiovascular [see Warnings and Precautions (5.1)] | - Sustained ventricular tachycardia (≥5 beats) - Cardiac rhythm disturbances not controlled or unresponsive to management - ECG changes consistent with ischemia or myocardial infarction or angina/chest pain - Cardiac tamponade | Permanently discontinue
Respiratory [see Warnings and Precautions (5.1)] | - O2 saturation <90% | Withhold until O2 saturation is >90%
Respiratory [see Warnings and Precautions (5.1)] | - Intubation for >72 hours | Permanently discontinue
Neurologic [see Warnings and Precautions (5.2)] | - Mental status changes, including moderate confusion or agitation | Withhold until completely resolved
Neurologic [see Warnings and Precautions (5.2)] | - Coma or toxic psychosis lasting >48 hours - Repetitive or difficult to control seizures | Permanently discontinue
Gastrointestinal [see Warnings and Precautions (5.1)] | Fecal immunochemical test (FIT) or fecal occult blood test (FOBT) positive | Withhold until FIT or FOBT negative
Gastrointestinal [see Warnings and Precautions (5.1)] | Bowel ischemia/perforation or GI bleeding requiring surgery | Permanently discontinue
Hepatic [see Warnings and Precautions (5.1)] | Signs of hepatic toxicity including liver pain or ≥ Grade 3 AST or ALT elevation | Withhold all further treatment for that course. Initiate a new course of treatment no sooner than 7 weeks after signs of hepatic toxicity have resolved and hospital discharge
Hepatic [see Warnings and Precautions (5.1)] | Hepatic failure | Permanently discontinue
Dermatologic [see Warnings and Precautions (5.5, 5.7)] | Bullous dermatitis or marked worsening of pre-existing skin condition | Withhold until all signs of bullous dermatitis have resolved
Infectious [see Warnings and Precautions (5.3)] | Sepsis syndrome, patient is clinically unstable | Withhold until sepsis syndrome has resolved, patient is clinically stable, infection is under treatment
Renal [see Warnings and Precautions (5.1, 5.4)] | Serum creatinine >4.5 mg/dL or a serum creatinine of ≥4 mg/dL in the presence of severe volume overload, acidosis, or hyperkalemia | Withhold until serum creatinine levels return to normal (<1.5 mg/dL) or baseline and fluid and electrolyte status are stable
Renal [see Warnings and Precautions (5.1, 5.4)] | Persistent oliguria, urine output of <10 mL/hr for 16-24 hours with rising SCr | Withhold until urine output >10 mL/hour with a decrease of serum creatinine >1.5 mg/dL or normalization of serum creatinine
Renal [see Warnings and Precautions (5.1, 5.4)] | Renal failure requiring dialysis >72 hours | Permanently discontinue

2.5 Preparation and Administration

Preparation

Reconstitute Proleukin using Sterile Water for Injection, USP. Do not reconstitute or dilute Proleukin with Bacteriostatic Water for Injection, or 0.9% Sodium Chloride Injection.

- Add 1.2 mL of Sterile Water for Injection, USP, by injecting the water along the walls of the vial and not directly on the lyophilized powder. The resulting concentration is 18 million IU (1.1 mg)/mL of Proleukin.
- The prepared solution is a clear, colorless to slightly yellow liquid.
- Slowly swirl the vial; do not shake.
- Withdraw the required dose of Proleukin and discard the vial with any unused portion.
- Use polyvinyl chloride bags for dilution of Proleukin and dilute using 5% Dextrose Injection to a concentration between 0.03 mg/mL and 0.07 mg/mL based on the required dose as follows:

Table 3: Recommended Proleukin Dilution
Dose | 5% Dextrose Volume
≤25.4 million IU (≤1.5 mg) | 25 mL
>25.4 million IU-60 million IU (>1.5 mg-3.5 mg) | 50 mL
>60 million IU (>3.5 mg) | 100 mL

Storage of Diluted Proleukin Infusion Solution

- Store under refrigeration at 2° to 8°C (36° to 46°F) for no more than 48 hours from the time of preparation to the end of the infusion.
- Protect from light.
- Do not freeze.
- Allow the diluted solution to come to room temperature prior to administration.

Administration

- Do not use in-line filters when administering Proleukin.
- Parenteral drug products should be inspected visually for particulate matter and discoloration prior to administration, whenever solution and container permit.
- Do not co-administer Proleukin with other drugs through the same intravenous line.
- Administer by intravenous infusion over 15 minutes.

3 DOSAGE FORMS AND STRENGTHS

For Injection: 22 million International Units (1.3 mg) of aldesleukin available as a white to off-white, lyophilized powder in a single-dose vial for reconstitution. When reconstituted, each mL contains 18 million International Units (1.1 mg) aldesleukin.

4 CONTRAINDICATIONS

- Severe Hypersensitivity Reactions

Proleukin is contraindicated in patients with a known history of severe hypersensitivity to aldesleukin or any component of the Proleukin formulation [see Adverse Reactions (6.2)].

- Organ Allografts

Proleukin is contraindicated in patients with organ allografts [see Warnings and Precautions (5.5)] .

- Significant Organ Impairment

Proleukin is contraindicated in patients with significant cardiac (including those with an abnormal cardiac ejection fraction, impaired wall motion, or significant coronary artery disease), pulmonary (including those with an FEV1 ≤ 2 liters or < 75% predicted for height and age), renal, hepatic, or CNS impairment [see Warnings and Precautions (5.1, 5.2, 5.4)] .

5 WARNINGS AND PRECAUTIONS

5.1 Capillary Leak Syndrome

Severe and life-threatening capillary leak syndrome (CLS) characterized by hypotension, dyspnea, edema, and hypoalbuminemia can occur with Proleukin, and can result in end organ toxicity including cardiac, respiratory, renal, hepatic toxicity, or death. Do not administer Proleukin to patients with significant cardiac, pulmonary, renal, or hepatic impairment. Avoid concomitant use of Proleukin with other products known to cause hypotension including antihypertensive drugs, those that cause renal toxicity, or hepatotoxicity.

CLS may begin immediately after Proleukin treatment is initiated. Monitor for signs and symptoms of CLS including assessments of vital signs, weight, fluid intake, albumin levels and urine output.

Withhold or discontinue Proleukin for failure to maintain organ perfusion as demonstrated by altered mental status, reduced urine output, oxygen saturation <90%, a fall in the systolic blood pressure below 90 mm Hg, or onset of cardiac arrhythmias. Initiate standard management for CLS, which may include intensive care [see Dosage and Administration (2.4), Use in Specific Populations (8.1)] .

5.2 Neurologic Toxicity

Proleukin can cause neurologic toxicities including mental status changes, speech difficulties, cortical blindness, limb or gait ataxia, hallucinations, agitation, obtundation, demyelinating polyneuropathy, and coma. Alterations in mental status may progress for several days before recovery begins. Permanent neurologic deficits have occurred. Radiological findings included multiple and, less commonly, single cortical lesions on MRI and evidence of demyelination. One case of possible cerebral vasculitis has been reported.

Monitor patients for signs and symptoms of neurological toxicity during Proleukin treatment. Withhold Proleukin in patients developing moderate to severe lethargy or somnolence; continued administration may result in coma. Permanently discontinue Proleukin for coma or toxic psychosis lasting >48 hours or for repetitive or difficult to control seizures [see Dosage and Administration (2.4)].

Evaluate and treat CNS metastases prior to initiation of Proleukin. If possible, avoid concomitant use of Proleukin with other product(s) with a known potential to cause neurotoxicity, and avoid Proleukin in patients with seizure disorders or abnormal intracranial imaging [see Contraindications (4), Adverse Reactions (6.1, 6.2)] . Concomitant use of Proleukin with other products that cause neurotoxicity may result in a greater risk of severe neurotoxicity.

5.3 Serious Infections Including Sepsis

Proleukin can cause impaired neutrophil function (reduced chemotaxis) and an increased risk of disseminated infection, including sepsis and bacterial endocarditis. Treat pre-existing bacterial infections prior to initiating Proleukin. Consider antibiotic prophylaxis in patients with indwelling central lines. Monitor patients for the development of signs and symptoms of infection during treatment and withhold Proleukin based on severity [see Dosage and Administration (2.4)].

5.4 Renal Toxicity

Serious renal toxicity, including oliguria and renal failure can occur with Proleukin [see Adverse Reactions (6.1, 6.2)] . Pre-existing renal impairment or coadministration of Proleukin with other products known to cause renal toxicity may increase this risk. If possible, avoid concomitant use of Proleukin with other product(s) with a known potential to cause renal toxicity. Serum creatinine should be ≤1.5 mg/dL before beginning Proleukin. Monitor serum creatinine at baseline and daily throughout each course of therapy. Withhold Proleukin, or permanently discontinue, based on severity [see Dosage and Administration (2.4)] .

5.5 Immune-mediated Adverse Reactions

Exacerbation of pre-existing autoimmune disease or initial presentation of autoimmune and inflammatory disorders has been reported following treatment with Proleukin. Immune-mediated adverse reactions, which may be severe or fatal, can occur in any organ system or tissue. These have included exacerbation of Crohn's disease, colitis, scleroderma, thyroiditis, inflammatory arthritis, diabetes mellitus, oculo-bulbar myasthenia gravis, crescentic IgA glomerulonephritis, cholecystitis, cerebral vasculitis, Stevens-Johnson syndrome, bullous pemphigoid, myocarditis, myositis, and neuritis including optic neuritis resulting in blindness [see Adverse Reactions (6.2)] .

Proleukin may increase the risk of allograft rejection in transplant patients [see Contraindications (4)] .

Hypothyroidism, sometimes preceded by hyperthyroidism, has been reported following Proleukin treatment. Evaluate thyroid function at baseline and periodically during treatment and initiate thyroid replacement therapy as clinically indicated.

Hyperglycemia and/or diabetes mellitus has been reported during Proleukin therapy. Monitor patients for hyperglycemia and initiate treatment with insulin as clinically indicated.

5.6 Embryo-Fetal Toxicity

Based on findings in an animal study and its mechanism of action, Proleukin may cause fetal harm or loss of pregnancy when administered to a pregnant woman. In pregnant rats, aldesleukin has been shown to have embryolethal effects at doses 27 times and maternal toxicities at doses 2.1 times the human exposure at the recommended clinical dose. Advise pregnant women of the potential risk to a fetus. Advise female patients of reproductive potential to use effective contraception during treatment with Proleukin [see Use in Specific Populations (8.1, 8.3)].

5.7 Serious Manifestations of Eosinophilia

Serious manifestations of eosinophilia involving eosinophilic infiltration of cardiac and pulmonary tissues can occur following Proleukin.

5.8 Delayed Adverse Reactions to Iodinated Contrast Media

A review of the literature revealed that 12.6% (range 11-28%) of 501 patients treated with various interleukin-2-containing regimens who were subsequently administered radiographic iodinated contrast media experienced acute, atypical adverse reactions. The onset of symptoms usually occurred within hours (most commonly 1 to 4 hours) following the administration of contrast media. These reactions include fever, chills, nausea, vomiting, pruritus, rash, diarrhea, hypotension, edema, and oliguria. These reactions may resemble the immediate side effects caused by interleukin-2 administration. Most events were reported to occur when contrast media was given within 4 weeks after the last dose of interleukin-2. These events were also reported to occur when contrast media was given several months after interleukin-2 treatment [see Adverse Reactions (6.2)] .

5.9 Severe Hypersensitivity Reactions

Proleukin can cause severe hypersensitivity reactions, including anaphylactic reactions. Permanently discontinue Proleukin in patients who experience a severe hypersensitivity reaction [see Contraindications (4), Adverse Reactions (6.2)].

5.10 Infusion-Related Reactions

Proleukin can cause fevers, chills, or rigors. Premedicate patients with an antipyretic prior to beginning Proleukin and continue during treatment as needed for fever [see Adverse Reactions (6.2)and Dosage and Administration (2.3)].

6 ADVERSE REACTIONS

The following clinically significant adverse reactions are described elsewhere in the labeling:

- Capillary Leak Syndrome [see Warnings and Precautions (5.1)].
- Neurotoxicity [see Warnings and Precautions (5.2)].
- Serious Infections Including Sepsis [see Warnings and Precautions (5.3)].
- Renal Toxicity [see Warnings and Precautions (5.4)].
- Immune-Mediated Adverse Reactions [see Warnings and Precautions (5.5)].
- Serious Manifestations of Eosinophilia [see Warnings and Precautions (5.7)].
- Severe Hypersensitivity Reactions [see Warnings and Precautions (5.9)].
- Infusion-Related Reactions [see Warnings and Precautions (5.10)] .

6.1 Clinical Trials Experience

Because clinical trials are conducted under widely varying conditions, adverse reaction rates observed in the clinical trials of a drug cannot be directly compared to rates in the clinical trials of another drug and may not reflect the rates observed in practice.

The safety of Proleukin was evaluated in a series of single and multicenter, controlled studies enrolling a total of 525 patients with metastatic renal cell carcinoma (mRCC studies) or metastatic melanoma (metastatic melanoma studies) [see Clinical Studies (14.1, 14.2)] .

In patients who received Proleukin in these studies, fatal adverse reactions occurred in 4% (11/255) of the patients with metastatic RCC, and 2% (6/270) of the patients with metastatic melanoma.

In these studies, >90% of patients had doses withheld for adverse reactions [see Dosage and Administration (2.4)].

The most common (≥30%) adverse reactions were hypotension, hyperbilirubinemia, dyspnea, rash, diarrhea, oliguria, chills, vomiting, thrombocytopenia, nausea, confusional state, and increased creatinine.

Table 4 summarizes adverse reactions that occurred in these studies.

Table 4: Adverse Reactions (≥10% all grades or ≥1% Grade 4) in Patients with Metastatic Renal Cell Carcinoma or Metastatic Melanoma (n=525) receiving Proleukin
Adverse Reaction | Proleukin N = 525
Adverse Reaction | All Grades (%) | Grade 4 (%)
General disorders
Chills | 52 | 0
Pyrexia | 29 | 1
Edema peripheral | 28 | 0
Malaise | 27 | 0
Asthenia | 23 | 0
Edema | 15 | 0
Pain | 12 | 0
Cardiac disorders
Hypotension | 71 | 3
Blood pressure fluctuation | Not documented | 1
Tachycardia | 23 | 0
Dilated veins | 13 | 0
Supraventricular tachycardia | 12 | 1
Ventricular tachycardia | <10 | 1
Cardiovascular disorder [Cardiovascular disorder: Electrocardiogram abnormal, cardiac failure congestive.] | 11 | 0
Myocardial infarction | <10 | 1
Arrhythmia | 10 | 0
Cardiac arrest | <10 | 1
Gastrointestinal disorders
Diarrhea | 67 | 2
Vomiting | 50 | 0
Nausea | 35 | 0
Stomatitis | 22 | <1
Decreased appetite | 20 | 0
Abdominal pain | 11 | 0
Abdominal distention | 10 | 0
Blood and lymphatic system disorders
Thrombocytopenia | 37 | 1
Anemia | 29 | 0
Leukopenia | 16 | 0
Disseminated intravascular coagulation | <10 | 1
Infections
Infections | 13 | 1
Sepsis | <10 | 1
Hepatobiliary disorders
Hyperbilirubinemia | 40 | 2
Aspartate aminotransferase increased | 23 | 1
Metabolic and nutritional disorders
Weight increased | 16 | 0
Acidosis | 12 | 1
Hypomagnesemia | 12 | 0
Hypocalcemia | 11 | <1
Blood alkaline phosphatase increased | 10 | 0
Nervous system disorders
Confusional state | 34 | 1
Stupor | <10 | 1
Coma | <10 | 2
Psychotic disorder | <10 | 1
Somnolence | 22 | 0
Anxiety | 12 | 0
Dizziness | 11 | 0
Respiratory, thoracic, and mediastinal disorders
Dyspnea | 43 | 1
Lung disorder [Lung disorder: Pulmonary congestion, rales, rhonchi.] | 24 | 0
Respiratory disorder [Respiratory disorder: Acute respiratory distress syndrome, lung infiltration, lung disorder, respiratory failure, endotracheal intubation.] | 11 | 3
Apnea | <10 | 1
Cough | 11 | 0
Rhinitis | 10 | 0
Skin and subcutaneous tissue disorders
Rash | 42 | 0
Pruritis | 24 | 0
Dermatitis exfoliative | 18 | 0
Renal and urinary disorders
Oliguria | 63 | 6
Blood creatinine increased | 33 | 1
Anuria | <10 | 5
Acute kidney injury | <10 | 1

Additional life-threatening adverse reactions (Grade 4) were reported by <1% of the 525 patients:

- Cardiac disorders: bradycardia, pericardial effusion, ventricular extrasystoles, myocardial ischemia, arrhythmia supraventricular, coronary artery disease, atrioventricular block second degree, endocarditis
- Eye disorders: mydriasis, pupillary disorder
- Gastrointestinal disorders: intestinal perforation, gastrointestinal hemorrhage, hematemesis, pancreatitis, diarrhea hemorrhagic
- General disorders and administration site conditions: hypothermia
- Infections and infestations: gangrene
- Metabolism and nutrition disorders: hyperuricemia
- Nervous system disorders: syncope, neuropathy peripheral, seizure, generalized tonic-clonic seizure
- Investigations: liver function tests abnormal, blood urea increased
- Psychiatric disorders: agitation, paranoia
- Renal and urinary disorders: renal failure, renal tubular necrosis
- Respiratory, thoracic and mediastinal disorders: respiratory acidosis, asthma, pulmonary edema, hyperventilation, hypoxia, hemoptysis, hypoventilation, pneumothorax
- Vascular disorders: shock, hemorrhage, phlebitis, thrombosis

Other Clinical Trial Experience

The following serious adverse reactions were reported in patients with RCC, melanoma, or other cancers treated with Proleukin-based regimens (n >1800 patients) using dosages other than the recommended dosage:

- Cardiovascular disorders: transient ischemic attacks, pericarditis
- Gastrointestinal disorders: duodenal ulcer; gastrointestinal necrosis, tracheo-esophageal fistula
- Nervous system disorders: meningitis, brain edema
- Renal and urinary disorders: nephritis (allergic)

In the same clinical population, the following fatal events each occurred with a frequency of <1%: hyperthermia malignant; cardiac arrest; myocardial infarction; pulmonary embolism; cerebrovascular accident; intestinal perforation; hepatic failure or renal failure; severe depression leading to suicide; pulmonary edema; respiratory arrest; respiratory failure. Patients with ECOG PS of 1 or higher had a higher treatment-related mortality and serious adverse events.

6.2 Postmarketing Experience

The following adverse reactions have been identified during post-approval use of Proleukin. Because these reactions are reported voluntarily from a population of uncertain size, it is not always possible to reliably estimate their frequency or establish a causal relationship to drug exposure.

- Blood and lymphatic system disorders: neutropenia, febrile neutropenia, eosinophilia, lymphopenia
- Cardiac disorders: cardiomyopathy, cardiac tamponade
- Endocrine disorders: hyperthyroidism
- Gastrointestinal disorders: gastritis, intestinal obstruction
- General disorders and administration site conditions: injection site necrosis
- Hepatobiliary disorders: hepatitis, hepatosplenomegaly, cholecystitis
- Immune system disorders: anaphylactic reaction, angioedema, urticaria
- Infections and infestations: pneumonia (bacterial, fungal, viral), endocarditis, cellulitis
- Metabolism and nutrition disorders: hyponatremia, hypophosphatemia
- Musculoskeletal and connective tissue disorders: myopathy, rhabdomyolysis
- Nervous system disorders: encephalopathy, extrapyramidal disorder, neuralgia
- Psychiatric disorders: insomnia
- Vascular disorders: hypertension, subdural hemorrhage, subarachnoid hemorrhage, cerebral hemorrhage, retroperitoneal hemorrhage

7 DRUG INTERACTIONS

Drug interaction studies with Proleukin have not been conducted. The drug interaction information described below have been observed post-marketing.

7.1 Effect of Other Drugs on Proleukin

Glucocorticoids

Avoid concomitant use of glucocorticoids. Coadministration with glucocorticoids may reduce aldesleukin antitumor effectiveness.

7.2 Effect of Proleukin on Other Drugs

Radiographic Iodinated Contrast Media

Monitor for delayed adverse reactions in patients receiving iodinated contrast media following Proleukin. Administration of radiographic iodinated contrast media following administration of interleukin-2 resulted in acute, atypical adverse reactions that resemble the immediate side effects caused by Proleukin in some patients [see Warnings and Precautions (5.8)] .

Effect on Cytochrome P-450 Substrates

For certain CYP substrates, minimal changes in the concentration may lead to serious adverse reactions. Monitor for toxicity or drug concentration changes of such CYP substrates when co-administered with Proleukin.

Aldesleukin causes release of cytokines [see Clinical Pharmacology (12.2)] that may suppress activity of CYP enzymes, resulting in increased exposure of CYP substrates.

8 USE IN SPECIFIC POPULATIONS

8.1 Pregnancy

Risk Summary

Based on findings in an animal study and its mechanism of action, Proleukin may cause fetal harm or loss of pregnancy when administered to a pregnant woman [see Clinical Pharmacology (12.1)]. Data on the use of Proleukin in pregnant women are limited and insufficient to assess the drug-associated risk of major birth defects, miscarriage, or other adverse maternal or fetal outcomes; however, development of capillary leak syndrome during pregnancy can lead to adverse fetal outcomes (see Clinical Considerations) .

Intravenous administration of aldesleukin to pregnant rats during the period of organogenesis resulted in embryo lethality at doses 27 times and maternal toxicities at doses 2.1 times the human exposure at the recommended clinical dose (see Data) . Advise pregnant women of the potential risk to a fetus.

In the U.S. general population, the estimated background risk of major birth defects and miscarriage in clinically recognized pregnancies is 2%–4% and 15–20%, respectively.

Clinical Considerations

Fetal/Neonatal Adverse Reactions

Capillary leak syndrome in women who are exposed to Proleukin during pregnancy may result in maternal hypotension and decreased placental perfusion. Severe or prolonged maternal hypotension and decreased placental perfusion can lead to intrauterine growth restriction, perinatal asphyxia, or fetal/neonatal demise. Monitor fetal and neonatal status in pregnant women who develop capillary leak syndrome associated with Proleukin.

Data

Animal Data

Aldesleukin has been shown to have embryolethal effects in rats when given in doses at 27 to 36 times the human dose (scaled by body weight). Significant maternal toxicities were observed in pregnant rats administered aldesleukin by IV injection at doses 2.1 to 36 times higher than the human dose during critical period of organogenesis.

8.2 Lactation

Risk Summary

There are no data on the presence of aldesleukin in either human or animal milk, the effects on the breastfed child, or the effects on milk production. Maternal cytokines are known to be present in human breast milk. Because of the potential for serious adverse reactions from Proleukin in a breastfed child, such as impaired immune function, advise women not to breastfeed during treatment.

8.3 Females and Males of Reproductive Potential

Based on animal data and mechanism of action, Proleukin may cause embryo-fetal harm [see Use in Specific Populations (8.1)].

Pregnancy Testing

Verify pregnancy status of females of reproductive potential prior to initiating Proleukin [see Use in Specific Populations (8.1)].

Contraception

Females

Advise females of reproductive potential to use effective contraception during treatment with Proleukin.

8.4 Pediatric Use

The safety and effectiveness of Proleukin have not been established in pediatric patients.

8.5 Geriatric Use

Clinical studies of Proleukin did not include sufficient numbers of patients 65 years of age and older to determine whether they respond differently from younger adult patients.

10 OVERDOSAGE

Exceeding the recommended dose of Proleukin has been associated with a more rapid onset of severe or life-threatening toxicities. Treat toxicities supportively; life-threatening toxicities may be ameliorated by the intravenous administration of dexamethasone.

11 DESCRIPTION

Aldesleukin is a human interleukin-2 lymphocyte growth factor produced by recombinant DNA technology using a genetically engineered E. colistrain containing an analog of the human interleukin-2 gene. It is a purified protein with a molecular weight of approximately 15,300 Da. This recombinant form differs from native interleukin-2 in the following ways: a) aldesleukin is not glycosylated; b) the molecule has no N-terminal alanine; c) the molecule has serine substituted for cysteine at amino acid position 125. Proleukin exists as biologically active, non-covalently bound microaggregates with an average size of 27 recombinant interleukin-2 molecules; the aggregation state of aldesleukin may differ compared to native interleukin-2.

The manufacturing process for aldesleukin involves fermentation in a defined medium containing tetracycline hydrochloride. The presence of tetracycline hydrochloride is not detectable in the final product.

Proleukin (aldesleukin) for injection is a sterile, preservative-free white to off-white, lyophilized powder, which has a cake-like appearance, supplied in single-dose vials for intravenous administration after reconstitution and dilution. When reconstituted with 1.2 mL Sterile Water for Injection, USP, each mL contains 18 million International Units (1.1 mg) aldesleukin, mannitol (50 mg), sodium dodecyl sulfate (0.19 mg), buffered with disodium hydrogen phosphate dihydrate (1.12 mg) and sodium dihydrogen phosphate dihydrate (0.19 mg) to a pH of 7.5 (range 7.2 to 7.8).

12 CLINICAL PHARMACOLOGY

12.1 Mechanism of Action

Aldesleukin is an interleukin-2 lymphocyte growth factor. The antitumor activity of aldesleukin has not been fully characterized. In vitrostudies performed on human cell lines show enhancement of lymphocyte mitogenesis and cytotoxicity, induction of killer cell activity [lymphokine-activated killer (LAK) and natural killer (NK) cells] and interferon gamma production, and proliferation of human interleukin-2-dependent cell lines.

Administration of aldesleukin in animals and humans produces multiple immunological effects in a dose-dependent manner. These effects include activation of cellular immunity and the production of cytokines including tumor necrosis factor, IL-1, and interferon gamma. In vivoexperiments in murine melanoma and sarcoma tumor models have shown inhibition of tumor growth.

12.2 Pharmacodynamics

Dose-dependent immunological effects including activation of cellular immunity with lymphocytosis, eosinophilia, and thrombocytopenia, and the production of cytokines including tumor necrosis factor, IL-1, and gamma interferon were observed following administration of aldesleukin in animals and humans.

Aldesleukin exposure-response relationships and the time course of pharmacodynamic response are unknown.

12.3 Pharmacokinetics

Aldesleukin serum concentrations change proportionally with the Proleukin dosage.

Distribution

Aldesleukin is rapidly distributed (distribution half-life of 13 minutes) into the extravascular space following a Proleukin intravenous infusion.

Elimination

The serum elimination half-life aldesleukin is 85 minutes in patients with cancer following a 5-minute intravenous infusion of Proleukin. The mean clearance rate of aldesleukin is 268 mL/min.

Metabolism

Aldesleukin is metabolized to amino acids in the proximal convoluted tubules of the kidney.

Excretion

Aldesleukin is primarily excreted in the kidney by both glomerular filtration and peritubular extraction. In the kidney it is metabolized and excreted into urine with little or no aldesleukin present.

12.6 Immunogenicity

The observed incidence of anti-drug antibodies is highly dependent on the sensitivity and specificity of the assay. Differences in assay methods preclude meaningful comparisons of the incidence of anti-drug antibodies in the studies described below with the incidence of anti-drug antibodies in other studies.

In clinical studies, using an enzyme-linked immunosorbent assay (ELISA), low titers of anti-aldesleukin antibodies were observed in 74% (57 of 77) of patients with metastatic renal cell carcinoma treated with an every 8-hour Proleukin regimen and in 66% (33 of 50) of patients with metastatic melanoma treated with a variety of intravenous regimens. In a separate study in 13 patients, following the first cycle of therapy, the geometric mean aldesleukin exposure (AUC) on Day 15 compared to Day 1 increased by 68% in 11 patients who developed anti-aldesleukin antibodies while no change was observed in the 2 antibody-negative patients. Overall, neutralizing antibodies were detected in 1 patient. Based on these data, the clinical relevance of anti-aldesleukin antibodies could not be assessed.

13 NONCLINICAL TOXICOLOGY

13.1 Carcinogenesis, Mutagenesis, Impairment of Fertility

The carcinogenic and genotoxic potential of aldesleukin have not been evaluated.

Animal fertility studies have not been conducted with aldesleukin.

13.2 Animal Toxicology and/or Pharmacology

Repeated doses of aldesleukin administered to animals intravenously resulted in dose-dependent extramedullary hematopoiesis and lymphoid hyperplasia.

14 CLINICAL STUDIES

14.1 Metastatic Renal Cell Cancer

The efficacy of Proleukin was evaluated in two hundred fifty-five patients with metastatic renal cell carcinoma (mRCC) in 7 clinical studies conducted at 21 institutions (mRCC studies). Eligible patients had an Eastern Cooperative Oncology Group (ECOG) Performance Status (PS) of 0 or 1 and normal organ function as determined by cardiac stress test, pulmonary function tests, and creatinine ≤1.5 mg/dL. Studies excluded patients with brain metastases, active infections, organ allografts, and diseases requiring steroid treatment. Not all patients in these studies received the recommended Proleukin dosing regimen.

The major efficacy outcome measure was objective response rate (ORR) determined by investigator assessment per ECOG response criteria for solid tumors (1982).

Efficacy results are summarized in Table 5.

Table 5: Proleukin Efficacy Results in mRCC Studies
 | Proleukin (n=255)
Objective Response Rate
ORR (95% CI), % | 15% (11, 20)
Complete Response (CR), % | 7%
Partial Response (PR), % | 8%
Duration of response (months)
Number of Patients Who Responded | n= 37
Median (months) | 54
Range (months) | 3, 131 [Denotes ongoing responses]

14.2 Metastatic Melanoma

The efficacy of Proleukin was evaluated in two hundred seventy patients with metastatic melanoma in 8 clinical studies conducted at 22 institutions (metastatic melanoma studies). Eligible patients had an Eastern Cooperative Oncology Group (ECOG) Performance Status (PS) of 0 or 1 and normal organ function as determined by cardiac stress test, pulmonary function tests, and creatinine ≤1.5 mg/dL. Studies excluded patients with brain metastases, active infections, organ allografts, and diseases requiring steroid treatment. Not all patients in these studies received the recommended Proleukin dosing regimen.

Patients with metastatic melanoma received a median of 18 of the 28 scheduled doses of Proleukin during the first course of therapy.

The major efficacy outcome measure was objective response rate (ORR) determined by investigator assessment per ECOG response criteria for solid tumors (1982).

Efficacy results are summarized in Table 6.

Table 6: Proleukin Efficacy Results in Metastatic Melanoma Studies
 | Proleukin (n=270)
Objective Response Rate
ORR (95% CI) | 16% (12, 21)
Complete Response (CR), % | 6%
Partial Response (PR), % | 10%
Duration of response (months)
Number of Patients Who Responded | n= 43
Median (months) (95% CI) | 9
Range (months) | 1, 122 [Denotes ongoing responses]

16 HOW SUPPLIED/STORAGE AND HANDLING

Proleukin®(aldesleukin) for injection is supplied in single-dose vials. Each vial contains 22 million International Units (1.3 mg) of Proleukin.

NDC 73776-022-01 Individually boxed single-dose vial

STORAGE AND HANDLING

Store unopened vials refrigerated at 2° to 8°C (36° to 46°F) in the original carton to protect from light.

Do not use beyond the expiration date printed on the vial. NOTE:This product contains no preservative.

17 PATIENT COUNSELING INFORMATION

Inform patients or caregivers of the following risks of Proleukin:

Capillary Leak Syndrome

Advise patients about the risk of capillary leak syndrome and to inform their healthcare provider immediately if they develop new or worsening symptoms of hypotension, dyspnea, or edema [see Warnings and Precautions (5.1)].

Neurotoxicity

Advise the patient to inform their healthcare provider immediately if they develop mental status changes, speech difficulties, blindness, ataxia, hallucinations, agitation, or experienced a seizure [see Warnings and Precautions (5.2)].

Serious Infections Including Sepsis

Advise patients to inform their healthcare provider immediately if they develop signs of infection or sepsis including fever, chills, weakness, dyspnea [see Warnings and Precautions (5.3)].

Immune-mediated Adverse Reactions

Advise patients that Proleukin can cause immune-mediated adverse reactions and can exacerbate pre-existing autoimmune disease. These immune-mediated adverse reactions can occur in any organ system or tissue. Proleukin may also increase the risk of allograft rejection in transplant patients. Advise patients to contact their healthcare provider for any new or worsening signs or symptoms [see Warnings and Precautions (5.5)] .

Hypothyroidism, sometimes preceded by hyperthyroidism, has been reported following Proleukin treatment. Evaluate thyroid function at baseline and periodically during treatment and initiate thyroid replacement therapy as clinically indicated.

Hyperglycemia and/or diabetes mellitus has been reported during Proleukin therapy. Monitor patients for hyperglycemia and initiate treatment with insulin as clinically indicated.

Serious Manifestations of Eosinophilia

Advise patients to inform their healthcare provider immediately if they develop serious symptoms of eosinophilia including new severe rash or dyspnea [see Warnings and Precautions (5.7)].

Delayed Adverse Reactions to Iodinated Contrast Media

Advise patients to inform their health care provider that they received Proleukin prior to undergoing imaging that requires iodinated contrast material [see Warnings and Precautions (5.8)].

Embryo-Fetal Toxicity

Advise females of reproductive potential to use effective contraception during treatment with Proleukin [see Warnings and Precautions (5.6), Use in Specific Populations (8.1, 8.3)] .

Proleukin may cause fetal harm. Advise females of reproductive potential to inform their healthcare provider of a known or suspected pregnancy [see Warnings and Precautions (5.6), Use in Specific Populations (8.1, 8.3)] .

Lactation

Advise females not to breastfeed during treatment with Proleukin [see Use in Specific Populations (8.2)] .

Hypersensitivity

Advise patients to inform their healthcare provider if they develop signs and symptoms of hypersensitivity reactions [see Warnings and Precautions (5.9)].

Manufactured by:
Iovance Biotherapeutics Manufacturing LLC
Philadelphia, PA 19112
U.S. License No. 2353

At
Boehringer Ingelheim Pharma
Biberach/Riss, Germany

For additional information, contact Iovance Biotherapeutics Manufacturing LLC. 1-844-845-IOVA (1-844-845-4682)

PROLEUKIN is a registered trademark.

© Iovance Biotherapeutics Manufacturing LLC.

PRINCIPAL DISPLAY PANEL - 1.3 mg Vial Carton

NDC 73776-022-01

Proleukin®
(aldesleukin)

for injection

22 million
International Units/Vial
(1.3 mg/vial)

Single-Dose Vial Discard Unused Portion
For Intravenous Infusion After Dilution
Refrigerate

Rx only

IOVANCE
BIOTHERAPEUTICS